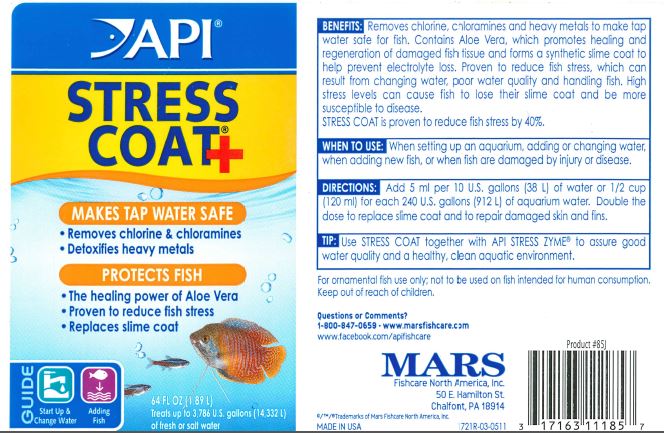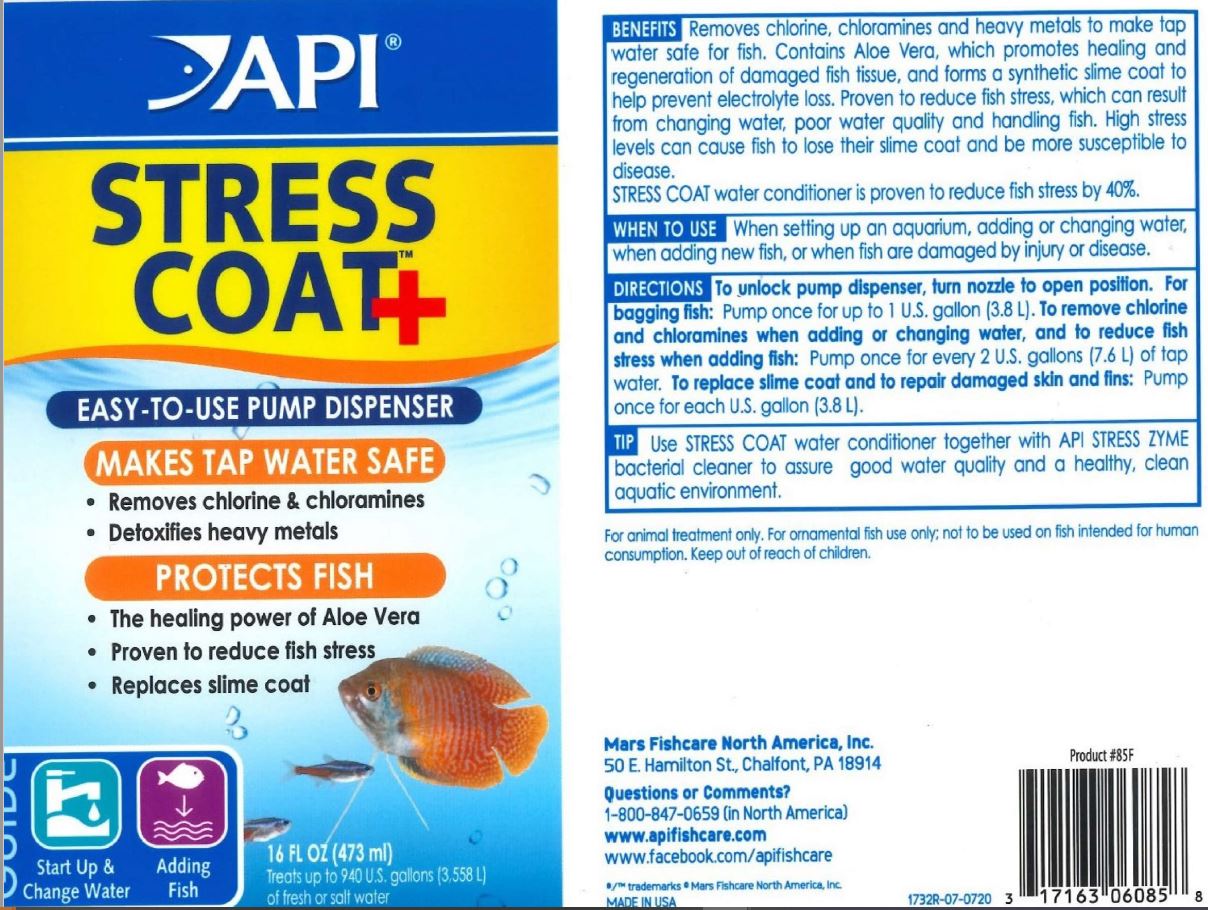 DRUG LABEL: API STRESS COAT
NDC: 17163-085 | Form: LIQUID
Manufacturer: MARS FISHCARE NORTH AMERICA, INC.
Category: animal | Type: OTC ANIMAL DRUG LABEL
Date: 20250321

ACTIVE INGREDIENTS: ALOE VERA LEAF 0.05 g/100 mL
INACTIVE INGREDIENTS: SODIUM THIOSULFATE; EDETIC ACID; POVIDONE, UNSPECIFIED; WATER

Drug Label

DESCRIPTION

BENEFITS:

Removes chlorine, chloramines and heavy metals to make tap water safe for fish. Contains Aloe Vera, which promotes healing and regeneration of damaged fish tissue and forms a synthetic slime coat to help prevent electrolyte loss. Proven to reduce fish stress, which can result from changing water, poor water quality and handling fish. High stress levels can cause fish to lose their slime coat and be more susceptible to disease.

STRESS COAT is proven to reduce fish stress by 40%.

INDICATIONS AND USAGE

WHEN TO USE:

When setting up an aquarium, adding or changing water, when adding new fish, or when fish are damaged by injury or disease.

DIRECTIONS:

Add 5 ml per 10 U.S. gallons (38 L) of water or 1/2 cup (120 ml) for each 240 U.S. gallons (912 L) of aquarium water. Double the dose to replace slime coat and to repair damaged skin and fins.

REFERENCES

TIP:

Use STRESS COAT together with API STRESS ZYME to assure good water quality and a healthy, clean aquatic environment.

WARNINGS AND PRECAUTIONS

For ornamental fish use only; not to be used on fish intended for human consumption.

Keep out of reach of children.

QUESTIONS

Questionsor Comments?

1-800-847-0659 www.marsfishcare.com

www.facebook.com/apifishcare

PACKAGE LABEL

API

STRESS

COAT+

MAKES TAP WATER SAFE

Removes chlorine and chloramines

Detoxifies heavy metals

PROTECTS FISH

the healing power of Aloe vera

Proven to reduce fish stress

Replaces slime coat

GUIDE

Start Up and

Change Water

Adding

Fish

64 FL OZ (1.89 L)

Treats up to 3,786 U.S. gallons (14,332 L)

of fresh or salt water

MADE IN USA